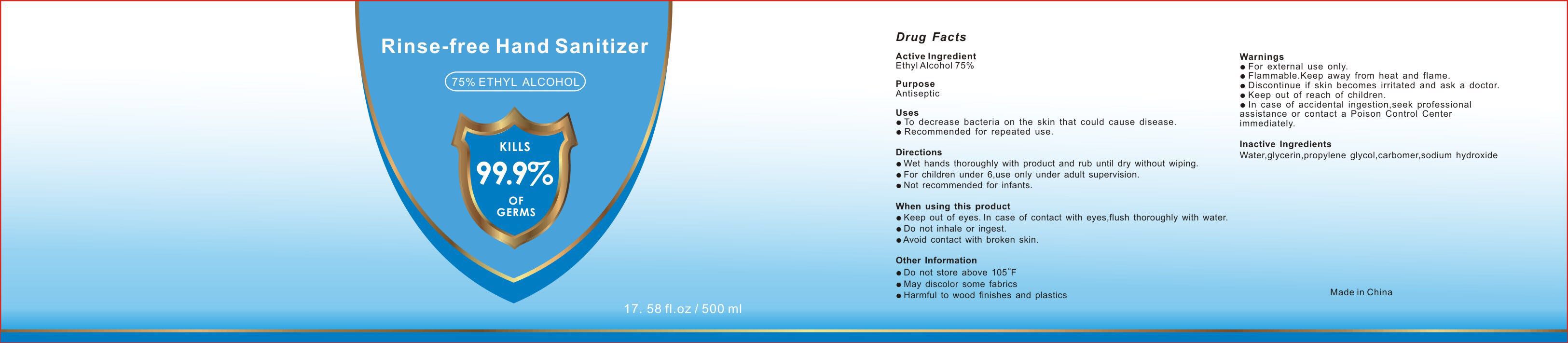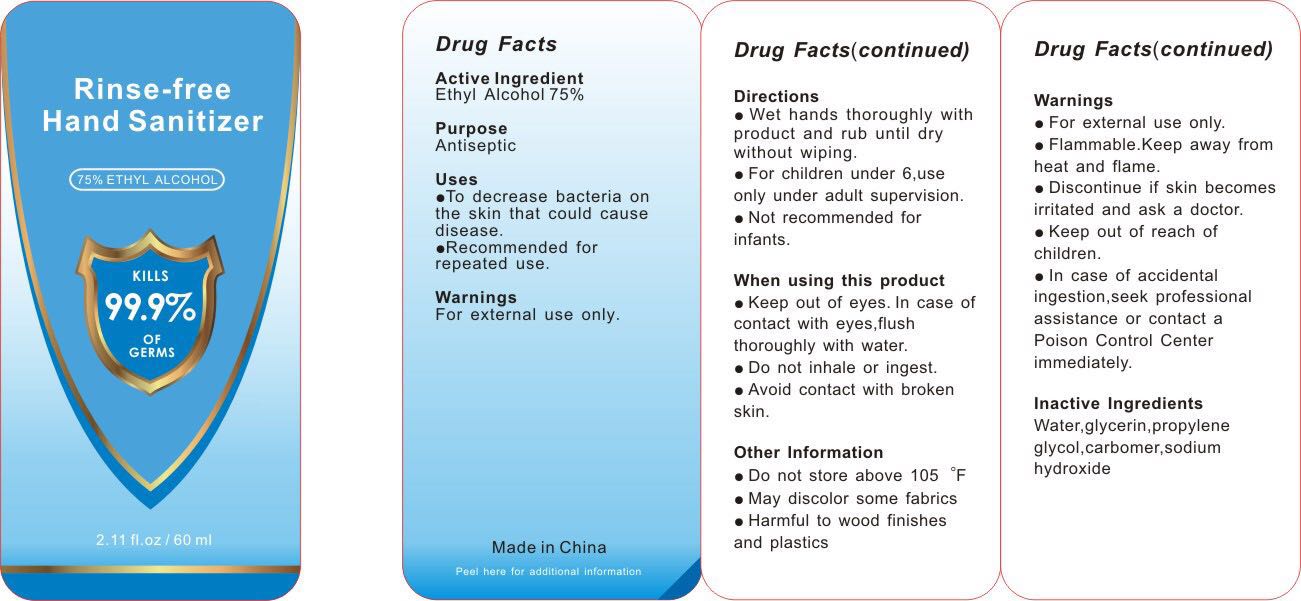 DRUG LABEL: Rinse-free Hand Sanitizer
NDC: 78345-006 | Form: GEL
Manufacturer: Ningbo Haishu Huasen Houseware Co.,Ltd
Category: otc | Type: HUMAN OTC DRUG LABEL
Date: 20200515

ACTIVE INGREDIENTS: ALCOHOL 68 mL/100 mL
INACTIVE INGREDIENTS: CARBOMER 1342; GLYCERIN; PROPYLENE GLYCOL; WATER; FD&C BLUE NO. 1; TROLAMINE; D&C RED NO. 33

Rinse-free Hand Sanitizer

Active Ingredient(s)

Ethyl Alcohol 75%

Purpose

Antiseptic

Use

To decrease bacteria on the skin that could cause diseasee.
Recommended for repeated use.

Warnings

For external use only.
Flammable. Keep away from heat and flame.
Discontinue if skin becomes irritated and ask a doctor.
Keep out of reach of children.
In case of accidental ingestion, seek professional assistance or contact a poison control center immediately.

Do not use

Do not inhale or ingest..

Do not store above 105°F.

WHEN USING

Keep out of eyes. In case of contact with eyes, flush thoroughly with water.
Do not inhale or ingest.
Avoid contact with broken skin.

STOP USE

/

Keep out of reach of children.
In case of accidental ingestion, seek professional assistance or contact a poison control center immediately.

Directions

Wet hands thoroughly with product and rub until dry without wiping.
For children under 6, use only under adult supervisiono.
Not recommended for infants

Other information

Do not store above 105°F
May discolor some fabrics
Harmful to wood finishes and plastics

Inactive ingredients

Water, glycerin, propylene glycol, carbomer, sodium hydroxide